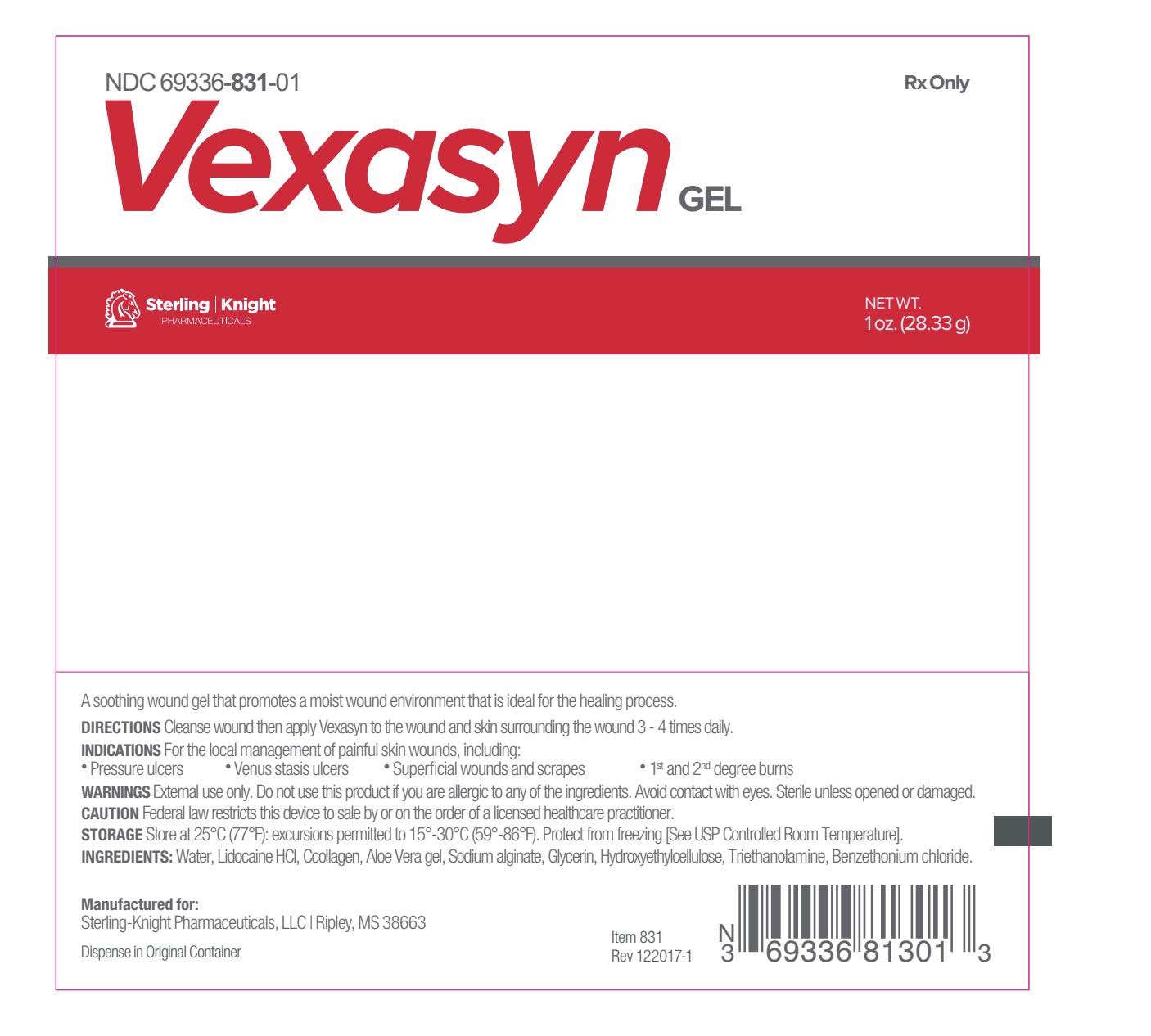 DRUG LABEL: Vexasyn
NDC: 69336-831
Manufacturer: Sterling-Knight Pharmaceuticals, LLC
Category: prescription | Type: HUMAN PRESCRIPTION DRUG LABEL
Date: 20180731
INACTIVE INGREDIENTS: WATER; LIDOCAINE HYDROCHLORIDE; SODIUM ALGINATE; GLYCERIN; HYDROXYETHYL CELLULOSE (100 MPA.S AT 2%); TROLAMINE; BENZETHONIUM CHLORIDE; ALOE VERA LEAF; BOVINE TYPE I COLLAGEN

Vexasyn Gel
Prescription Only | Rx Only

Vexasyn is a soothing wound gel that promotes a moist wound environment that is ideal for the healing process.

Directions:

Cleanse wound then apply Vexasyn to the wound and skin surrounding the wound 3 - 4 times daily.

Indications:

For the local management of painful skin wounds, including:
• Pressure ulcers
• Venus stasis ulcers
• Superficial wounds and scrapes
• 1st and 2nd degree burns

Warnings:

External use only. Do not use this product if you are allergic to any of the ingredients. Avoid contact with eyes. Sterile unless opened or damaged.

Caution:

Federal law restricts this device to sale by or on the order of a licensed healthcare practitioner.

Storage:

Store at 25°C (77°F): excursions permitted to 15°-30°C (59°-86°F). Protect from freezing [See USP Controlled Room Temperature].

Ingredients:

Ingredients: Water, Lidocaine HCl, Collagen, Aloe Vera gel, Sodium alginate, Glycerin, Hydroxyethylcellulose, Triethanolamine, Benzethonium chloride.

CALL YOUR DOCTOR ABOUT SIDE EFFECTS.
Call your doctor about side effects. You may report side effects to Sterling Knight Pharmaceuticals, LLC at 1-888-460-1531 or the FDA at 1-800-FDA-1088.

How Supplied

Vexasyn wound gel is supplied as a gel in:
1 oz. (28.33g) tube, NDC 69336-831-01

Distributed By:
Sterling-Knight Pharmaceuticals, LLC
Ripley, MS 38663

Rev 121517-1